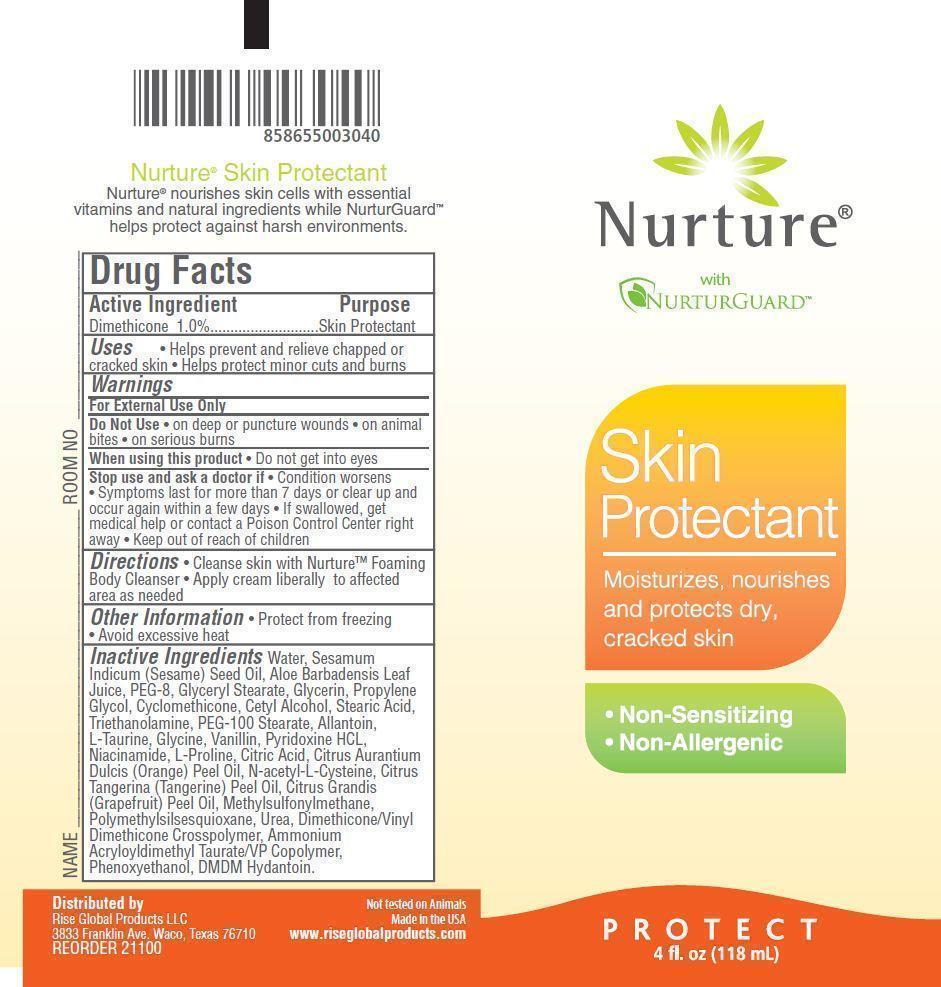 DRUG LABEL: Nurture Skin Protectant
NDC: 59973-002 | Form: CREAM
Manufacturer: Rise Global Products
Category: otc | Type: HUMAN OTC DRUG LABEL
Date: 20130816

ACTIVE INGREDIENTS: DIMETHICONE 10 mg/1 mL
INACTIVE INGREDIENTS: ALLANTOIN; ALOE VERA LEAF; AMMONIUM ACRYLOYLDIMETHYLTAURATE/VP COPOLYMER; SESAME OIL; CETYL ALCOHOL; CITRIC ACID MONOHYDRATE; ORANGE OIL; CITRUS MAXIMA FRUIT RIND OIL; MANDARIN OIL; GLYCERIN; CYCLOMETHICONE; DIMETHICONE/VINYL DIMETHICONE CROSSPOLYMER (SOFT PARTICLE); DMDM HYDANTOIN; GLYCERYL MONOSTEARATE; GLYCINE; PROLINE; TAURINE; DIMETHYL SULFONE; NIACINAMIDE; POLYETHYLENE GLYCOL 400; PEG-100 STEARATE; PHENOXYETHANOL; POLYMETHYLSILSESQUIOXANE (4.5 MICRONS); PROPYLENE GLYCOL; PYRIDOXINE HYDROCHLORIDE; STEARIC ACID; TROLAMINE; VANILLIN; UREA; WATER

Active Ingredient Purpose

Dimethicone 1.0%..............Skin Protectant

PURPOSE

Long-lasting nourishing formula that helps prevent dry, cracked skin.

- Non-Sensitizing
- Non-Allergenic

Keep out of reach of children

If swallowed, get medical help or contact a Poison Control Center right away

Uses

Temporarily protects and helps relieve chapped or cracked skin.

Beneficial for face, hands, body and legs

Warnings

For External Use Only

Do Not Use

- on deep or puncture wounds
- on animal bites
- on serious burns

When using this product

- Do not get into eyes

Stop use and ask a doctor if

- condition worsens
- symptoms last for more than 7 days or clear up and occur again within a few days

Directions

- Cleanse skin with Nurture(TM) Foaming Body Cleanser
- Apply cream liberally to affected area as needed

Other Information

- Protect from freezing
- Avoid excessive heat

Inactive Ingredients

Water, canola oil, alow barbadensis leaf juice, PEG-8, glyceryl stearate, glycerin, propylene glycol, cyclomethicone, cetyl alcohol, stearic acid, triethanolamine, PEG-100 Stearate, allantoin, pyridoxine HCL, niacinamide, glycine, L-taurine, N-acetyl-L-cysteine, methylsulfonylmethane, L-proline, vanillin, citrus aurantium dulcis (orange) peel oil, citrus tangerina (tangerine) peel oil, citrus grandis (grapefruit) peel oil, dimethicone/vinyl dimethicone crosspolymer, citric acid, urea, polymethylsilsesquioxane, ammonium acryloyldimethyl taurate/vp copolymer, phenoxyethanol, DMDM hydantoin.